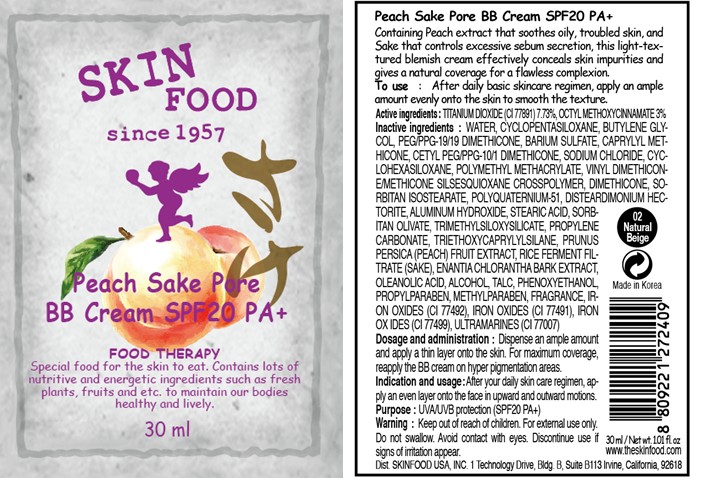 DRUG LABEL: PEACH SAKE PORE BB
NDC: 76214-016 | Form: CREAM
Manufacturer: SKINFOOD CO., LTD.
Category: otc | Type: HUMAN OTC DRUG LABEL
Date: 20110907

ACTIVE INGREDIENTS: TITANIUM DIOXIDE 2.32 mL/30 mL; OCTINOXATE 0.9 mL/30 mL
INACTIVE INGREDIENTS: WATER; CYCLOMETHICONE 5; BUTYLENE GLYCOL; BARIUM SULFATE; SODIUM CHLORIDE; CYCLOMETHICONE 6; DIMETHICONE; ALUMINUM HYDROXIDE; STEARIC ACID; SORBITAN OLIVATE; PROPYLENE CARBONATE; TALC; PHENOXYETHANOL; PEACH; ALCOHOL; PROPYLPARABEN; METHYLPARABEN; ANNICKIA CHLORANTHA BARK; OLEANOLIC ACID

Drug Facts

Active ingredients: TITANIUM DIOXIDE 7.73%, OCTINOXATE 3%

Inactive ingredients:
WATER, CYCLOPENTASILOXANE, BUTYLENE GLYCOL, PEG/PPG-19/19 DIMETHICONE, BARIUM SULFATE, CAPRYLYL METHICONE, CETYL PEG/PPG-10/1 DIMETHICONE, SODIUM CHLORIDE, CYCLOHEXASILOXANE, POLYMETHYL METHACRYLATE, VINYL DIMETHICONE/METHICONE SILSESQUIOXANE CROSSPOLYMER, DIMETHICONE, SORBITAN ISOSTEARATE, POLYQUATERNIUM-51, DISTEARDIMONIUM HECTORITE, ALUMINUM HYDROXIDE, STEARIC ACID, SORBITAN OLIVATE, TRIMETHYLSILOXYSILICATE, PROPYLENE CARBONATE, TRIETHOXYCAPRYLYLSILANE, PRUNUS PERSICA (PEACH) FRUIT EXTRACT, RICE FERMENT FILTRATE (SAKE), ENANTIA CHLORANTHA BARK EXTRACT, OLEANOLIC ACID, ALCOHOL, TALC, PHENOXYETHANOL, PROPYLPARABEN, METHYLPARABEN, FRAGRANCE, IRON OXIDES (CI 77492), IRON OXIDES (CI 77491), IRON OXIDES (CI 77499), ULTRAMARINES (CI 77007)

Purpose: UVA/UVB protection (SPF20 PA+)

Warnings:
For external use only.
Do not swallow.
Avoid contact with eyes.
Discontinue use if signs of irritation appear.

Keep out of reach of children:
Keep out of reach of children.

INDICATIONS AND USAGE

Indication and usage: After your daily skin care regimen, apply an even layer onto the face in upward and outward motions.

Dosage and administration:
Dispense an ample amount and apply a thin layer onto the skin.
For maximum coverage, reapply the BB cream on hyper pigmentation areas.